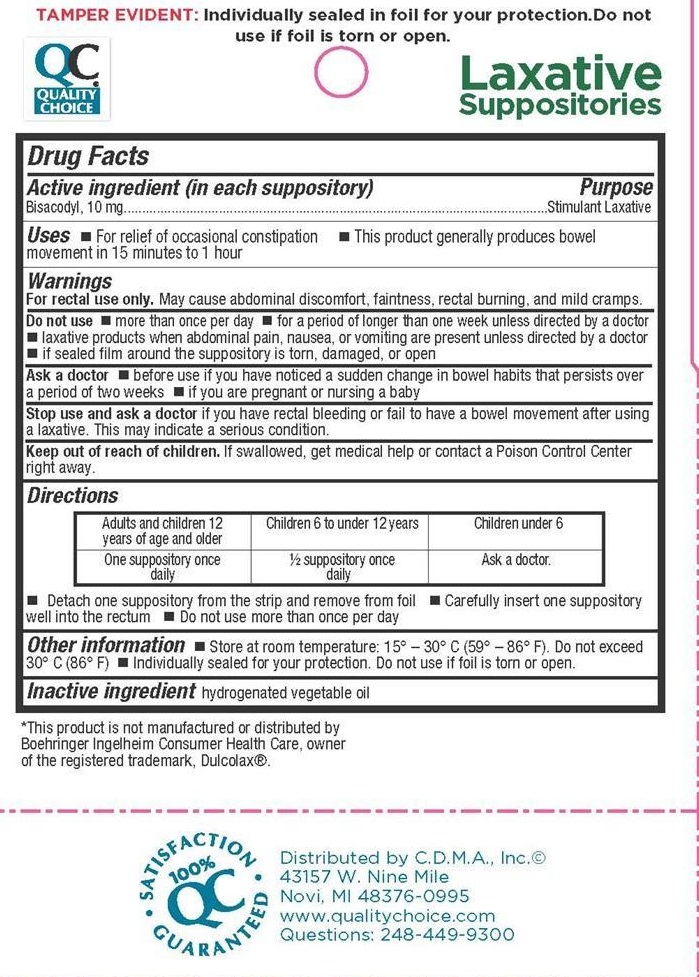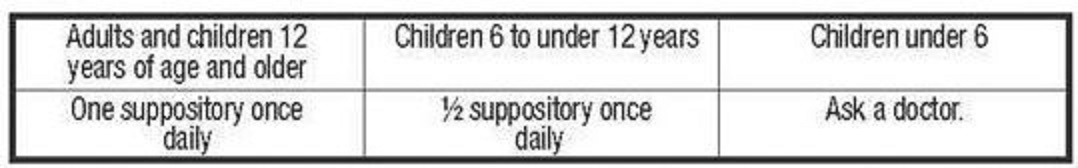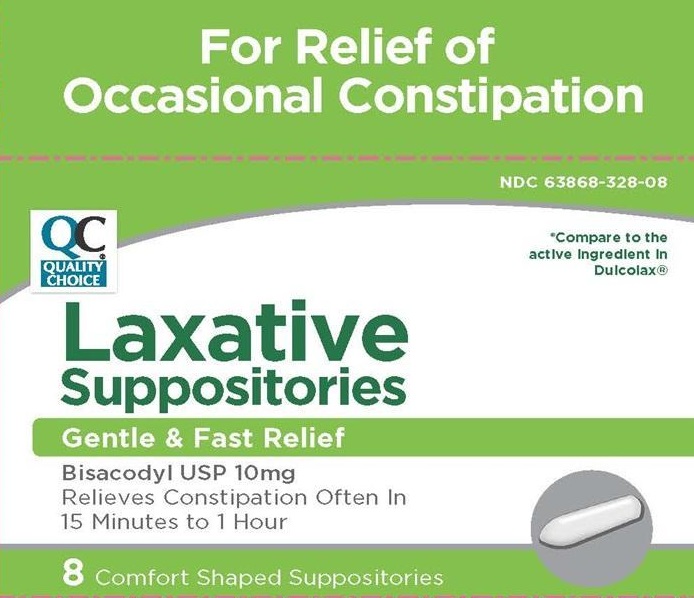 DRUG LABEL: Laxative
NDC: 63868-328 | Form: SUPPOSITORY
Manufacturer: Chain Drug Marketing Association, Inc.
Category: otc | Type: HUMAN OTC DRUG LABEL
Date: 20210519

ACTIVE INGREDIENTS: BISACODYL 10 mg/1 1
INACTIVE INGREDIENTS: FAT, HARD

Chain Drug Marketing Association - Bisacodyl Suppository

Active ingredient

Active ingredient (in each Suppository)

Bisacodyl, 10 mg

Purpose

Stimulant Laxative

Keep out of reach of children.

If swallowed, get medical help or contact a Poison Control Center right away.

Uses

- For relief of occasional constipation
- This product generally produces bowel movement in 15 minutes to 1 hour

Do not use

- more than once per day
- for a period of longer than one week unless directed by a doctor
- laxative products when abdominal pain, nausea, or vomiting are present unless directed by a doctor
- if sealed film around the suppository is torn, damaged, or open

Ask a doctor

- before use if you have noticed a sudden change in bowel habits that persists over a period of two weeks
- if you are pregnant or nursing a baby

Stop use and ask a doctor

if you have rectal bleeding or fail to have a bowel movement after using a laxative. This may indicate a serious condition.

Directions

- Detach one suppository from the strip and remove from foil
- Carefully insert one suppository well into the rectum
- Do not use more than once per day

Other information

- Store at room temperature: 15° - 30° C (59° - 86° F) Do not exceed 30° C (86° F)
- Individually sealed for your protection. Do not use if foil is torn or open.

Inactive ingredients

hydrogenated vegetable oil

Warnings

For rectal use only.

May cause abdominal discomfort, faintness, rectal burning, and mild cramps.